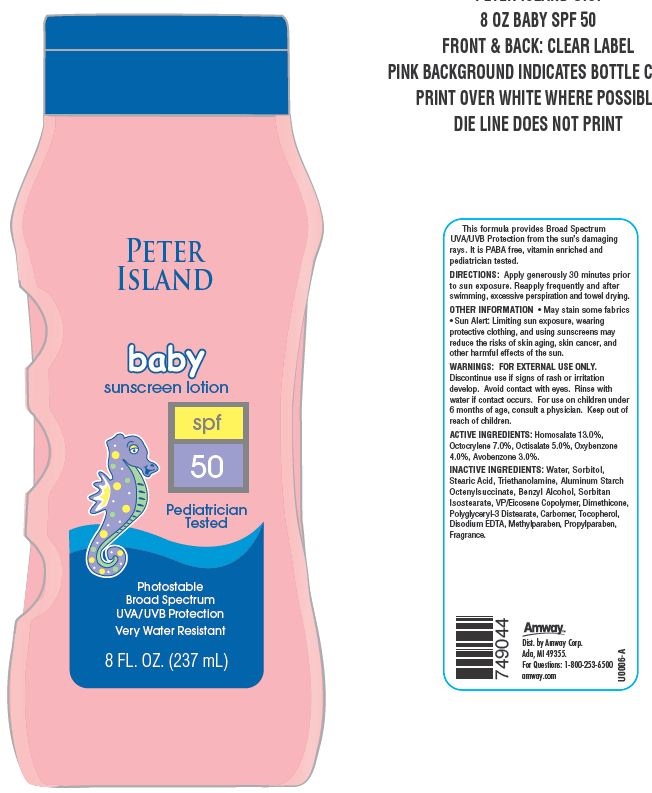 DRUG LABEL: Peter Island Baby Sunscreen
NDC: 10056-706 | Form: LOTION
Manufacturer: Access Business Group LLC
Category: otc | Type: HUMAN OTC DRUG LABEL
Date: 20130708

ACTIVE INGREDIENTS: HOMOSALATE 13 g/100 g; OXYBENZONE 4 g/100 g; AVOBENZONE 3 g/100 g; OCTISALATE 5 g/100 g; OCTOCRYLENE 7 g/100 g
INACTIVE INGREDIENTS: METHYLPARABEN; PROPYLPARABEN; WATER; SORBITOL; STEARIC ACID; ALUMINUM STARCH OCTENYLSUCCINATE; BENZYL ALCOHOL; SORBITAN ISOSTEARATE; DIMETHICONE; TOCOPHEROL; EDETATE DISODIUM; TROLAMINE

ACTIVE INGREDIENTS:

Homosalate 13.0%

Octocrylene 7.0%

Octisalate 5.0%

Oxybenzone 4.0%

Avobenzone 3.0%

WARNINGS:

FOR EXTERNAL USE ONLY.
Avoid contact with eyes. Rinse with water if contact occurs.

STOP USE

Discontinue use if signs of rash or irritation develop.

ASK DOCTOR

For use on children under the age of 6 months consult a physician.

Keep out of reach of children.

DIRECTIONS:

Apply generously and evenly 30 minutes before sun exposure. Reapply frequently and after swimming, excessive perspiration and towel drying.

OTHER INFORMATION

- May stain some fabrics
- Sun Alert: Limiting sun exposure, wearing protective clothing, and using sunscreens may reduce the risks of skin aging, skin cancer, and other harmful effects of the sun.

This formula provides Broad Spectrum UVA/UVB protection from the sun's damaging rays. It is PABA free, vitamin enriched and pediatrician tested.

Principal Display Panel

PETER ISLAND

baby

Sunscreen lotion

spf 50

Pediatrician Tested

Photostable

Broad Spectrum

UVA/UVB Protection

Very Water Resistant

8 FL.OZ. (237 mL)

INACTIVE INGREDIENTS:

Water, Sorbitol, Stearic Acid, Triethanolamine, Aluminum Starch Octenylsuccinate, Benzyl Alcohol, Sorbitan Isostearate, VP/Eicosene Copolymer, Dimethicone, Polyglyceryl-3 Distearate, Carbomer, Tocopherol, Disodium EDTA, Methylparaben, Propylparaben, Fragrance.